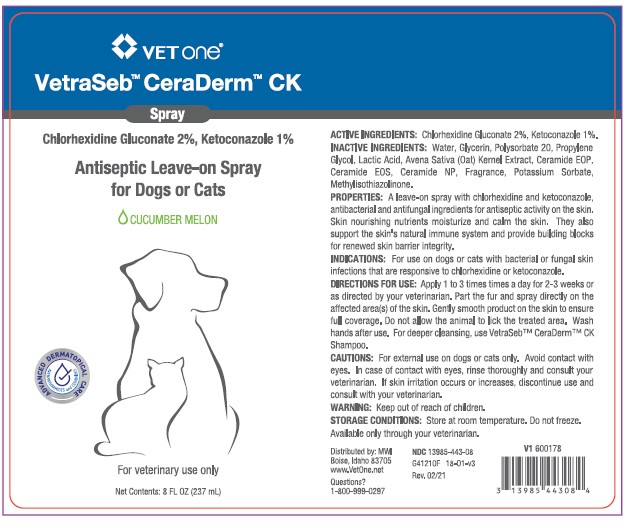 DRUG LABEL: VetraSeb CeraDerm
NDC: 13985-443 | Form: SPRAY
Manufacturer: MWI/VETONE
Category: animal | Type: OTC ANIMAL DRUG LABEL
Date: 20210414

ACTIVE INGREDIENTS: CHLORHEXIDINE GLUCONATE 20 mg/1 mL; KETOCONAZOLE 10 mg/1 mL
INACTIVE INGREDIENTS: WATER; GLYCERIN; POLYSORBATE 20; PROPYLENE GLYCOL; LACTIC ACID; AVENANTHRAMIDES; CERAMIDE 1; CERAMIDE EOS; CERAMIDE NP; POTASSIUM SORBATE; METHYLISOTHIAZOLINONE

DESCRIPTION

VetraSeb™ CeraDerm™ CK

Antiseptic Leave-on Spray for Dogs or Cats

CUCUMBER MELON

ACTIVE INGREDIENTS: Chlorhexidine Gluconate 2%, Ketoconazole 1%.

INACTIVE INGREDIENTS: Water, Glycerin, Polysorbate 20, Propylene Glycol, Lactic Acid, Avena Sativa (Oat) Kernal Extract, Ceramide EOP, Ceramide EOS, Ceramide NP, Fragrance, Potassium Sorbate, Methylisothiazolinone.

PROPERTIES: A leave-on spray with chlorhexidine and ketoconazole, antibacterial and antifungal ingredients for antiseptic activity on the skin. Skin nourishing nutrients moisturize and calm the skin. They also support the skin's natural immune system, and provide building blocks for renewed skin barrier integrity.

INDICATIONS AND USAGE

INDICATIONS: For use on dogs or cats with bacterial or fungal skin infections that are responsive to chlorhexidine or ketoconazole.

DIRECTIONS FOR USE: Apply 1 to 3 times per day for 2-3 weeks or as directed by your veterinarian. Part the fur and spray directly onto the affected area(s) of the skin. Gently smooth product on the skin to ensure full coverage. Do not allow the animal to lick the treated area. Wash hands after use. For deeper cleansing, use VetraSeb™ CeraDerm™ CK Shampoo.

WARNINGS AND PRECAUTIONS

CAUTIONS: For external use on dogs or cats only. Avoid contact with eyes. In case of contact with eyes, rinse thoroughly and consult your veterinarian. If skin irritation occurs or increases, discontinue use and consult with your veterinarian.

WARNING: Keep out of reach of children.

STORAGE AND HANDLING

STORAGE CONDITIONS: Store at room temperature. Do not freeze.

Available only through your veterinarian.

Distributed by: MWI

Boise, Idaho 83705

www.VetOne.net

QUESTIONS?

1-800-999-0297

PRINCIPAL DISPLAY PANEL - 8 OUNCE (237 mL) Bottle

VETONE®

VetraSeb™ CeraDerm™ CK

Spray

Chlorhexidine Gluconate 2%, Ketoconazole 1%

Antiseptic Leave-on Spray for Dogs or Cats

CUCUMBER MELON

For veterinary use only

Net Contents: 8 FL.OZ. (237 mL)